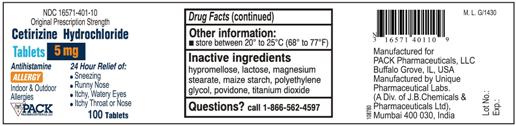 DRUG LABEL: Cetirizine Hydrochloride
NDC: 67668-161 | Form: TABLET
Manufacturer: Unique Pharmaceutical Laboratories
Category: otc | Type: HUMAN OTC DRUG LABEL
Date: 20091218

ACTIVE INGREDIENTS: Cetirizine Hydrochloride 5 mg/1 1
INACTIVE INGREDIENTS: hypromellose; lactose; magnesium stearate; starch, corn; polyethylene glycol; povidone; titanium dioxide

Cetirizine Hydrochloride Tablets, 5 mg, Allergy

Active Ingredients

Active Ingredients (in each tablet) Purpose
Cetirizine HCl 5 mg.....................................................................................Antihistimine

Uses

Temporarily relieves these symptoms due to hay fever or other upper respiratory allergies:

- runny nose
- sneezing
- itchy, watery eyes
- itching of the nose or throat

Warnings

Do Not Use if you have ever had an allergic reaction to this product or any of its ingredients or to an antihistamine containing hydroxyzine.

Ask a doctor before use if you have liver or kidney disease. Your doctor should determine if you need a different dose.

Ask a doctor or pharmacist before use if you are taking tranquilizers or sedatives.

When using this product

- drowsines may occur
- avoid alcoholic drinks
- alcohol, sedatives, and tranquilizers may increase drowsiness
- be careful when driving a motor vehicle or operating machinary.

Stop use and ask a doctor if an allergic reaction to this product occurs. Seek medical help right away.

If pregnant or breast-feeding:

- if breast-feeding: not recommended
- if pregnant: ask a health professional before use.

Keep out of reach of children.

In case of overdose, get medical help or contact Poison Control Center right away.

Directions

Adults and children 6 years and over | 1 to 2 tablets once daily depending upon severity of symptoms; do not take more than 2 tablets in 24 hours.
Adults 65 years and over | 1 tablet1 tablet once a day; do not take more than 1 tablet in 24 hours.
Children under 6 years of age | Ask a doctor
Consumers with liver or kidney disease | Ask a doctor

Other Information

store between 20° to 25°C (68° to 77°F)

Inactive Ingredients

hypromellose, lactose, magnesium stearate, maize starch, polyethylene glycol, povidone, titanium dioxide.

Questions?

Call 1-866-562-4597

Manufactured for Unique Pharmaceutical Laboratories (A Div. of J. B. Chemicals & Pharmaceuticals Ltd.), Mumbai, INDIA.

Manufactured by Unique Pharmaceutical Laboratories (A Div. of J. B. Chemicals & Pharmaceuticals Ltd.), Mumbai, INDIA.

Cetirizine Hydrochloride Tablets 5 mg Container Label

NDC 16571-401-10

Original Prescription Strength

Cetirizine Hydrochloride

Tablets 5 mg

Antihistamine 24 Hour Relief of:

- Sneezing
- Runny Nose
- Itchy, Watery Eyes
- Itchy Throat or Nose

100 Tablets

Allergy

Indoor & Outdoor

Allergies

PACK PHARMACEUTICALS LLC